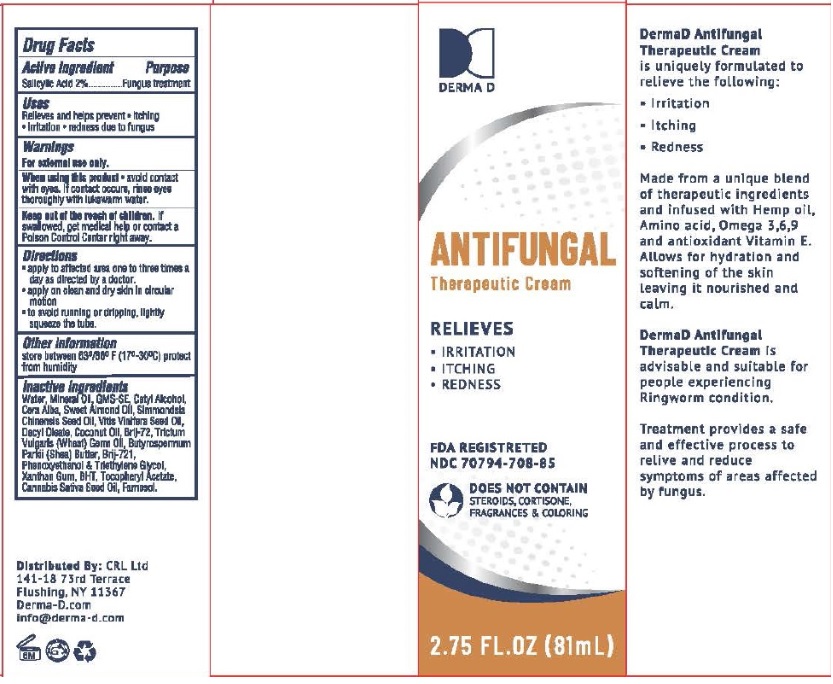 DRUG LABEL: DermaD ANTIFUNGAL Therapeutic
NDC: 70794-708 | Form: CREAM
Manufacturer: Chen Cohen Industries Inc.
Category: otc | Type: HUMAN OTC DRUG LABEL
Date: 20250529

ACTIVE INGREDIENTS: SALICYLIC ACID 20 mg/1 g
INACTIVE INGREDIENTS: WATER; MINERAL OIL; CETYL ALCOHOL; WHITE WAX; ALMOND OIL; JOJOBA OIL; GRAPE SEED OIL; DECYL OLEATE; COCONUT OIL; WHEAT GERM OIL; STEARETH-2; STEARETH-21; SHEA BUTTER; PHENOXYETHANOL; TRIETHYLENE GLYCOL; XANTHAN GUM; .ALPHA.-TOCOPHEROL; BUTYLATED HYDROXYTOLUENE; FARNESOL; CANNABIS SATIVA SEED

Drug Facts

Active Ingredient

Salicylic Acid....2%

Purpose

Fungus treatment

Uses

Relieves and helps prevent

- itching
- irritation
- redness due to jock itch

Warnings

For external use only

When using this product

avoid contact with eyes. If contact occurs, rinse eyes thoroughly with lukewarm water.

Keep out of reach of children

If swallowed, get medical help or contact a Poison Control Center right away.

Directions

- Apply to the affected area one to three times a day or as directed by a doctor.
- Apply on clean and dry skin in circular motion.
- To avoid running or dripping, lightly squeeze the tube.

Other Information

Store between 63°/80°F (17-30C)

Protect from humidity.

Inactive Ingredients

water, mineral oil, gms-se, Cetyl alcohol, cera alba, sweet almond oil, simmondsia chinensis seed oil, vitis vinifera seed oil, decyl oleate, coconut oil, brij-72, Trictum vulgaris (wheat) germ oil, butyrospermum parkii (shea) butter, brij-721, phenoxyethanol, triethylene glycol, Xanthan gum, BHT, Tocopheryl Acetate, Cannabis Sativa Seed Oil, farnesol

Principal Display Panel

NDC 70794-708-85

DERMAD ANTIFUNGAL Therapeutic Cream

RELIEVES

- IRRITATION
- ITCHING
- REDNESS

FDA REGISTERED

DOES NOT CONTAIN STEROIDS, CORTISONE, FRAGRANCES AND COLORING

2.75 FL. OZ (81 mL)